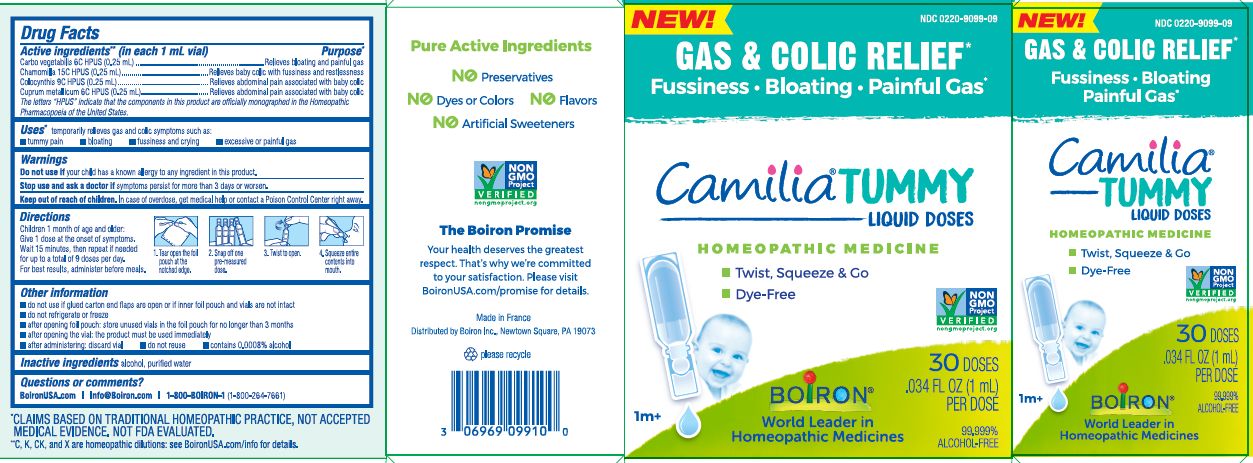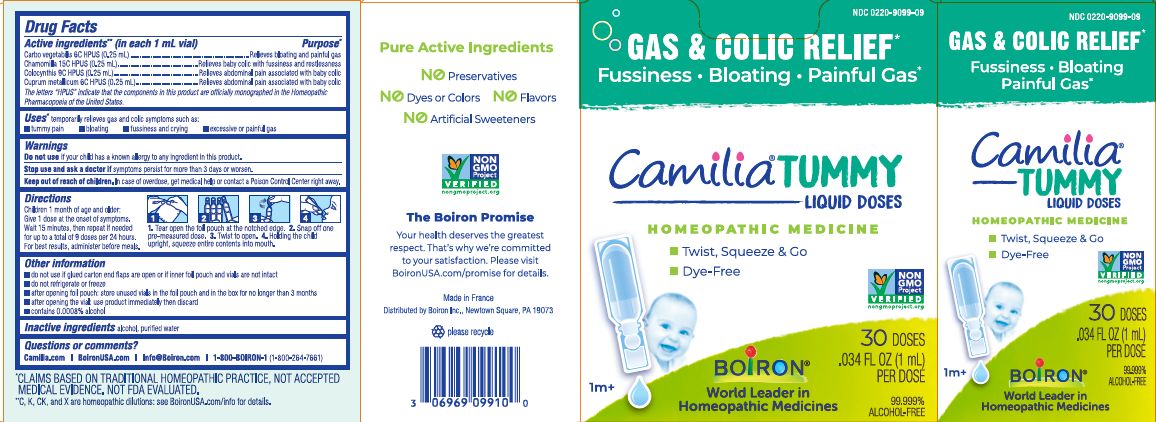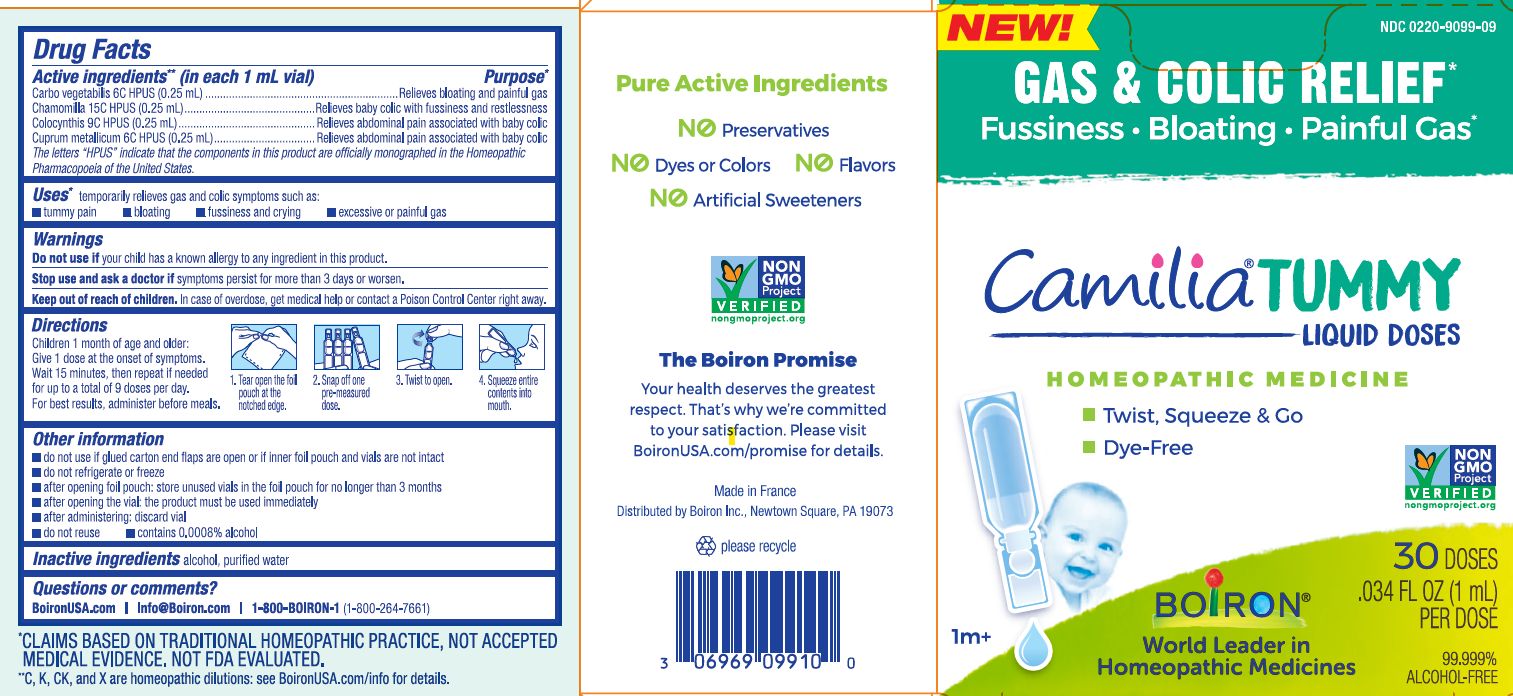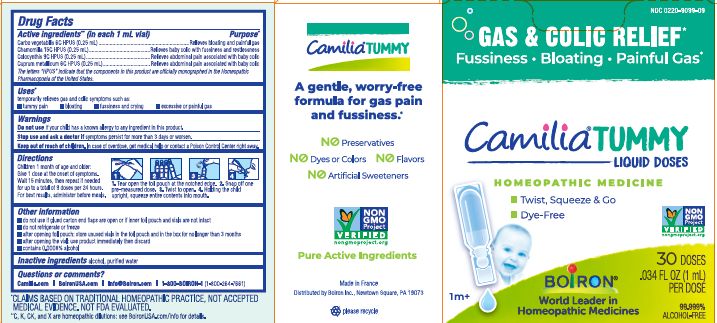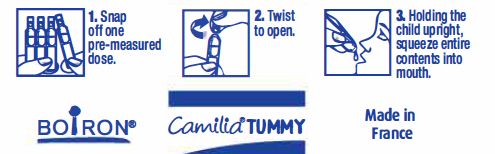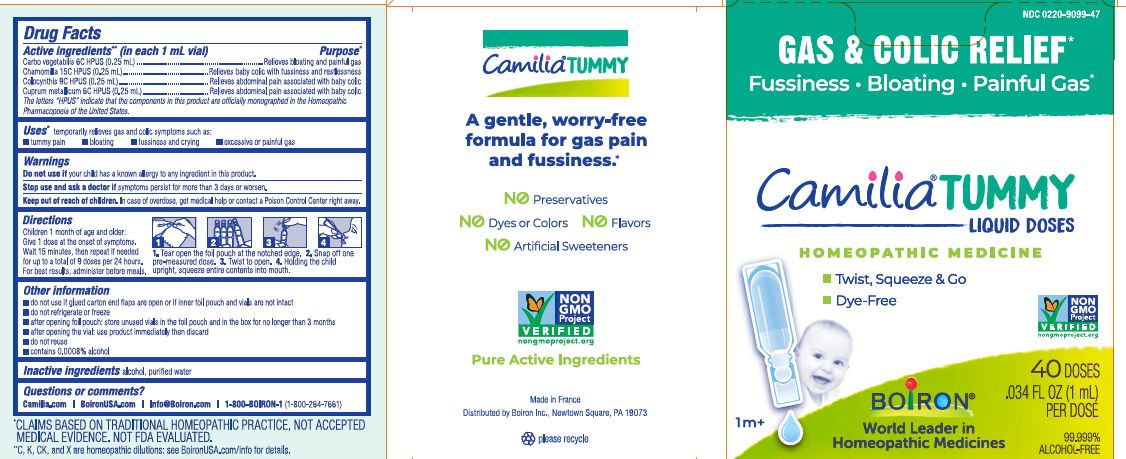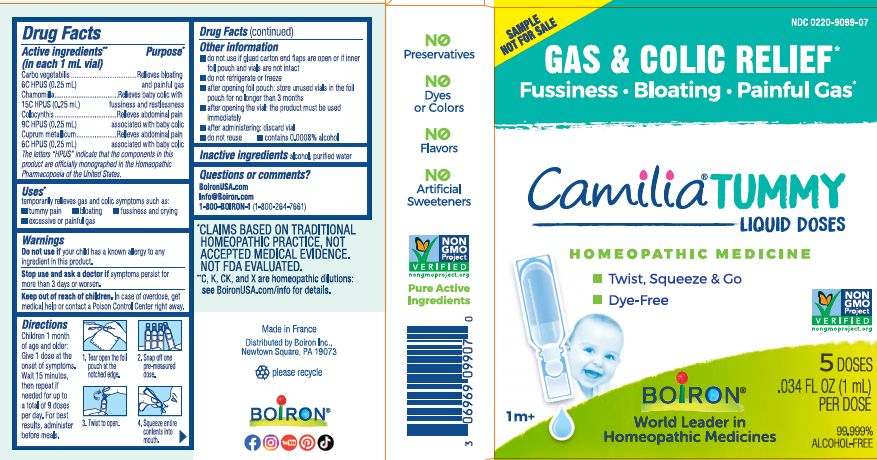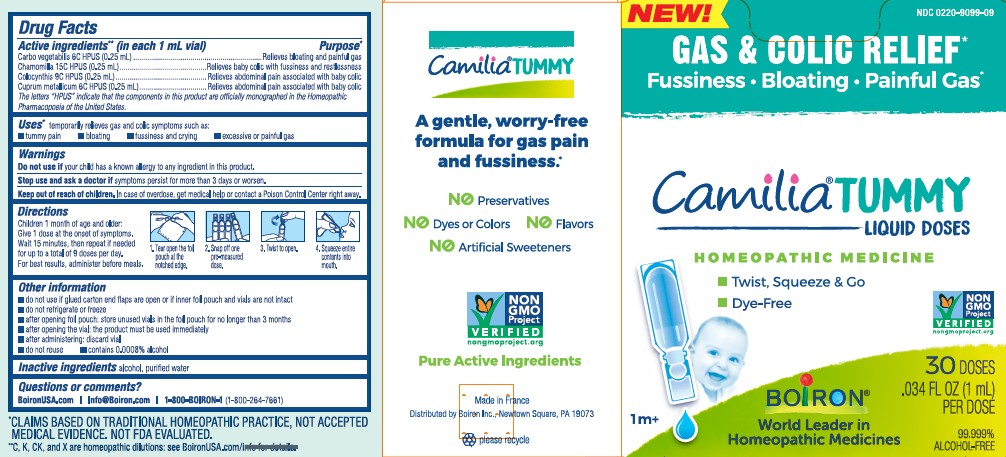 DRUG LABEL: Camilia Tummy
NDC: 0220-9099 | Form: LIQUID
Manufacturer: Boiron
Category: homeopathic | Type: HUMAN OTC DRUG LABEL
Date: 20250916

ACTIVE INGREDIENTS: CITRULLUS COLOCYNTHIS FRUIT PULP 9 [hp_C]/1 1; COPPER 6 [hp_C]/1 1; ACTIVATED CHARCOAL 6 [hp_C]/1 1; MATRICARIA CHAMOMILLA 15 [hp_C]/1 1
INACTIVE INGREDIENTS: ALCOHOL; WATER

Camilia Tummy

Active ingredients** (in each 1 mL vial)

Carbo vegetabilis 6C HPUS (0.25 mL)

Chamomilla 15C HPUS (0.25 mL)

Colocynthis 9C HPUS (0.25 mL)

Cuprum metallicum 6C HPUS (0.25 mL)

The letters "HPUS" indicate that the components in this product are officially monographed in the Homeopathic Pharmacopoeia of the United States.

Purpose*

Carbo vegetabilis 6C HPUS (0.25 mL) ... Relieves bloating and painful gas

Chamomilla 15C HPUS (0.25 mL) ... Relieves baby colic with fussiness and restlessness

Colocynthis 9C HPUS (0.25 mL) ... Relieves abdominal pain associated with baby colic

Cuprum metallicum 6C HPUS (0.25 mL) ... Relieves abdominal pain associated with baby colic

Uses*

temporarily relieves gas and colic symptoms such as:

- tummy pain
- bloating
- fussiness and crying
- excessive or painful gas

Do not use if your child has a known allergy to any ingredient in this product.

Stop use and ask a doctor if symptoms persist for more than 3 days or worsen.

Keep out of reach of children. In case of overdose, get medical help or contact a Poison Control Center right away.

Directions

Children 1 month of age and older: Give 1 dose at the onset of symptoms. Wait 15 minutes, then repeat if needed for up to a total of 9 doses per 24 hours. For best results, administer before meals.

1. Tear open the foil pouch at the notched edge.

2. Snap off one pre-measured dose.

3. Twist to open.

4. Holding the child upright, squeeze entire contents into mouth.

INACTIVE INGREDIENT

alcohol, purified water

QUESTIONS

Camilia.com

BoironUSA.com

Info@Boiron.com

1-800-BOIRON-1 (1-800-264-7661)

Made in France

Distributed by Boiron, Inc. Newtown Square, PA 19073

do not use if glued carton end flaps are open or if inner foil pouch and vials are not intact

do not refrigerate or freeze

after opening foil pouch: store unused vials in the foil pouch and in the box for no longer than 3 months

after opening the vial: use product immediately then discard

contains 0.0008% alcohol

GAS & COLIC RELIEF*

Fussiness Bloating Painful Gas*

5 Doses

30 Doses

40 Doses

0.034 FL OZ (1 mL) per dose

99.999% ALCOHOL-FREE

*CLAIMS BASED ON TRADITIONAL HOMEOPATHIC PRACTICE NOT ACCEPTED MEDICAL EVIDENCE. NOT FDA EVALUATED.
**C,K,CK, and X are homeopathic dilutions: see BoironUSA.com/info for details.